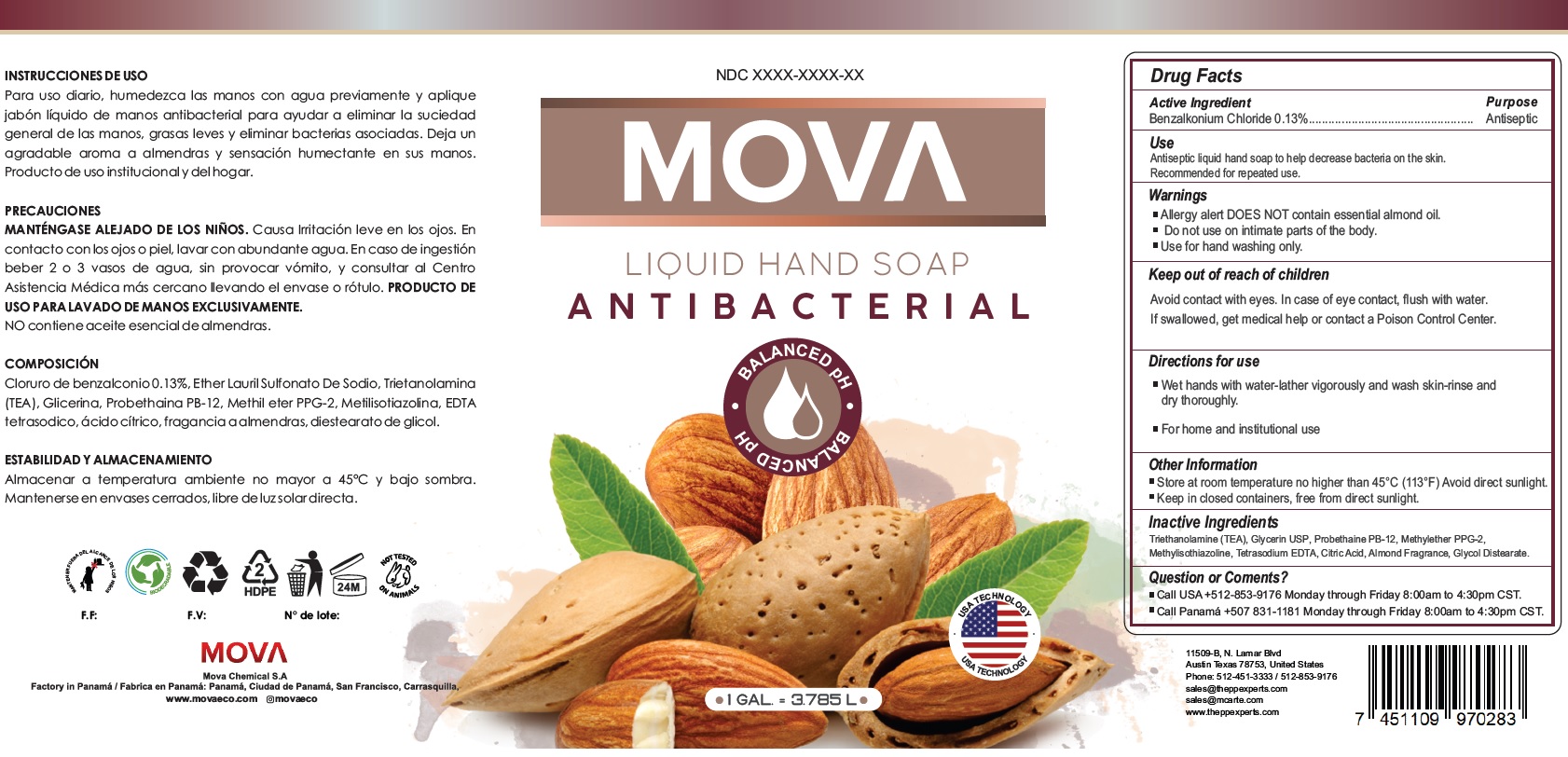 DRUG LABEL: Mova Liquid Hand Antibacterial
NDC: 81235-001 | Form: GEL
Manufacturer: Mova Chemical S.A
Category: otc | Type: HUMAN OTC DRUG LABEL
Date: 20230104

ACTIVE INGREDIENTS: BENZALKONIUM CHLORIDE 1.3 mg/1 mL
INACTIVE INGREDIENTS: TROLAMINE; GLYCERIN; METHYLISOTHIAZOLINONE; EDETATE SODIUM; CITRIC ACID MONOHYDRATE; GLYCOL DISTEARATE

Mova Liquid Hand Soap Antibacterial

Active Ingredient

Benzalkonium Chloride 0.13%

Purpose

Antiseptic

Use

Antiseptic liquid hand soap to help decrease bacteria on the skin.
Recommended for repeated use.

Warnings

- Allergy alert DOES NOT contain essential almond oil.

Do not use

- on intimate parts of the body.
- Use for hand washing only.

Keep out of reach of children

Avoid contact with eyes. In case of eye contact, flush with water. If swallowed, get medical help or contact a Poison Control Center.

Directions for use

- Wet hands with water-lather vigorously and wash skin-rinse and dry thoroughly.
- For home and institutional use

Other Information

- Store at room temperature no higher than 45°C (113°F) Avoid direct sunlight.
- Keep in closed containers, free from direct sunlight.

Inactive Ingredients

Triethanolamine (TEA), Glycerin USP, Probethaine PB-12, Methylether PPG-2, Methylisothiazoline, Tetrasodium EDTA, Citric Acid, Almond Fragrance, Glycol Distearate.

Question or Coments?

- Call USA +512-853-9176 Monday through Friday 8:00am to 4:30pm CST.
- Call Panama +507 831-1181 Monday through Friday 8:00am to 4:30pm CST.